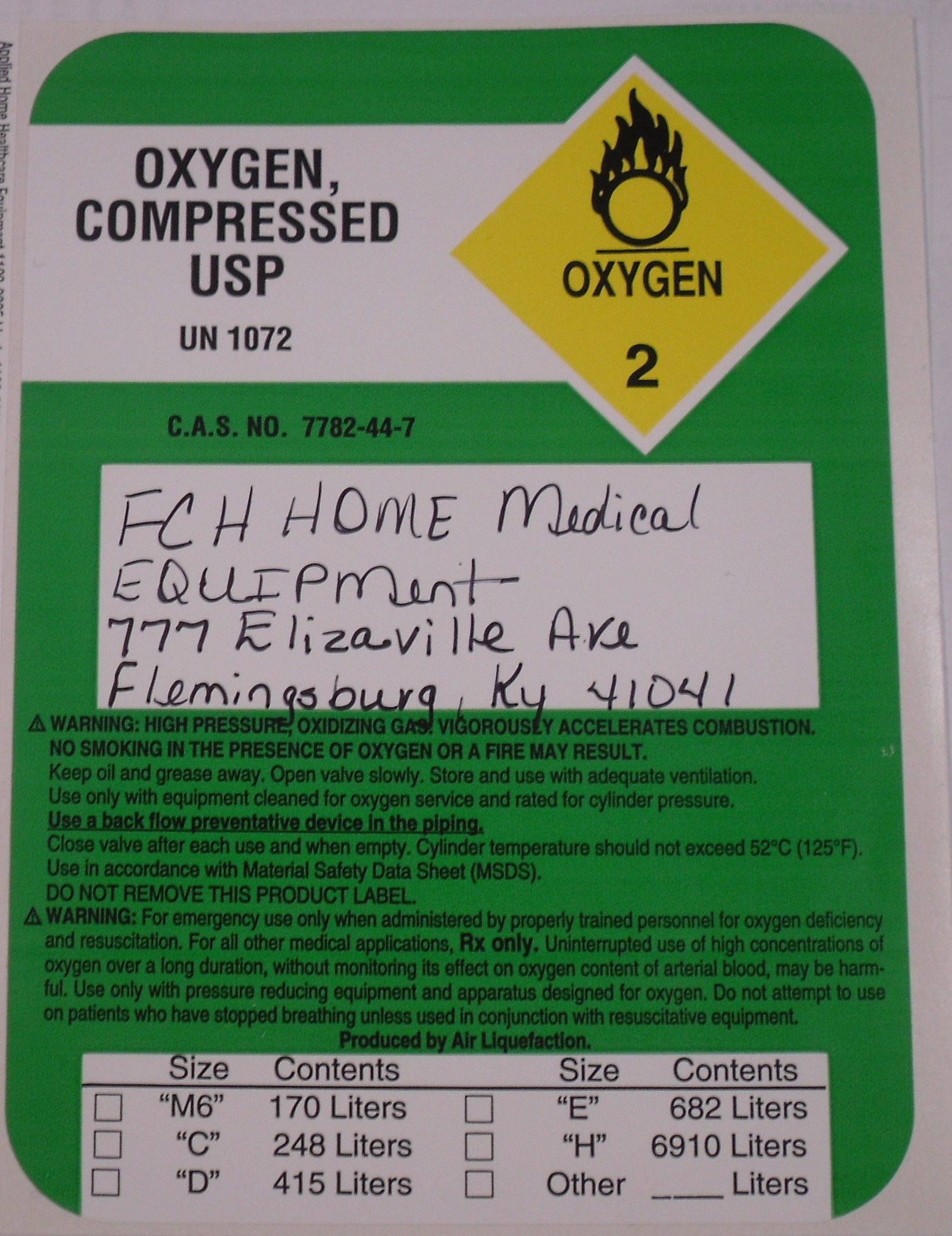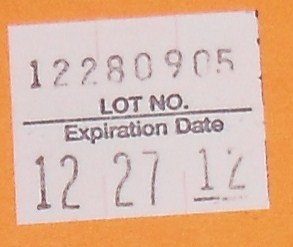 DRUG LABEL: Oxygen
NDC: 63755-0001 | Form: GAS
Manufacturer: Fleming County Hospital Home Medical Equipment
Category: prescription | Type: HUMAN PRESCRIPTION DRUG LABEL
Date: 20100106

ACTIVE INGREDIENTS: Oxygen 99 L/100 L

Oxygen